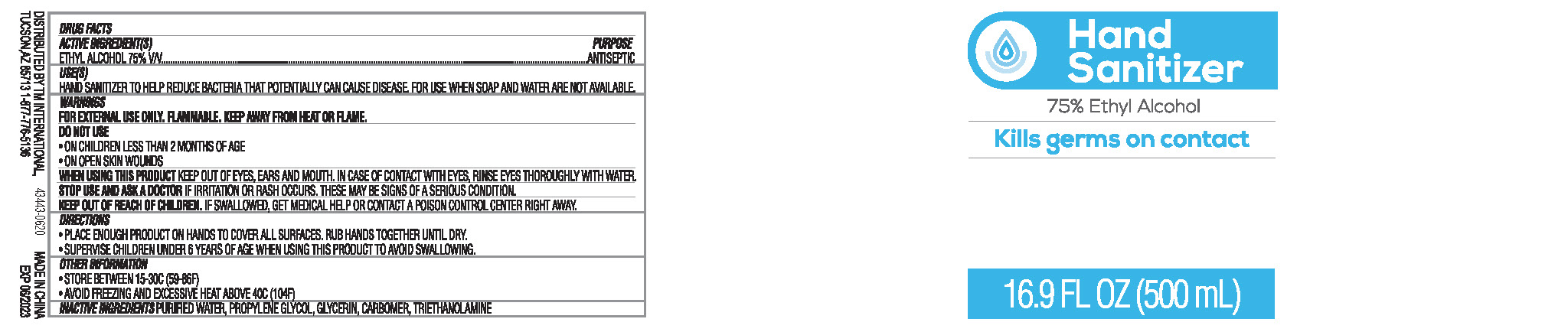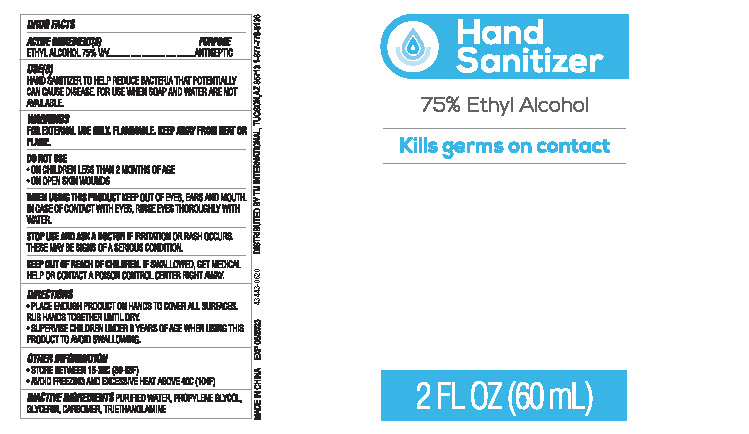 DRUG LABEL: Hand Sanitizer
NDC: 75427-006 | Form: GEL
Manufacturer: Jinhua City Wellmae Cosmetics Co., Ltd.
Category: otc | Type: HUMAN OTC DRUG LABEL
Date: 20220119

ACTIVE INGREDIENTS: ALCOHOL 75 mL/100 mL
INACTIVE INGREDIENTS: PROPYLENE GLYCOL; CARBOMER COPOLYMER TYPE A; WATER; TROLAMINE; GLYCERIN

75427-006
Hand Sanitizer

Active Ingredient(s)

ETHYL ALCOHOL 75% V/V

Use

HAND SANITIZER TO HELP REDUCE BACTERIA THAT POTENTILLY CAN CAUSE DISEASE, FOR USE WHEN SOAP AND WATER ARE NOT AVAILABLE.

Do not use

●ON CHILDREN LESS THAN 2 MONTHS OF AGE

●ON OPEN SKIN WOUNDS

WHEN USING

KEEP OUT OF EYES, EARS AND MOUTH. IN CASE OF CONTACT WITH EYES, RINSE EYES THOROUGHLY WITH WATER.

STOP USE

IF IRRITATION OR RASH OCCURS. THESE MAY BE SIGNS OF A SERIOUS CONDITION.

KEEP OUT OF REACH OF CHILDREN

IF SWALLOWED, GET MEDICAL HELP OR CONTACT A POISON CONTROL CENTER RIGHT AWAY.

Directions

●PLACE ENOUGH PRODUCT ON HANDS TO COVER ALL SURFACES. RUB HANDS TOGETHER UNTIL DRY.

●SUPERVISE CHILDREN UNDER 6 YEARS OF AGE WHEN USING THIS PRODUCT TO AVOID SWALLOWING.

Other information

●STORE BETWEEN 15-30C (59-86F)

●AVOID FREEZING AND EXCESSIVE HEAT ABOVE 40C (104F)

Inactive ingredients

PURIFIED WATER, PROPYLENE GLYCOL, GLYCERIN, CARBOMER, TRIETHANOLAMINE